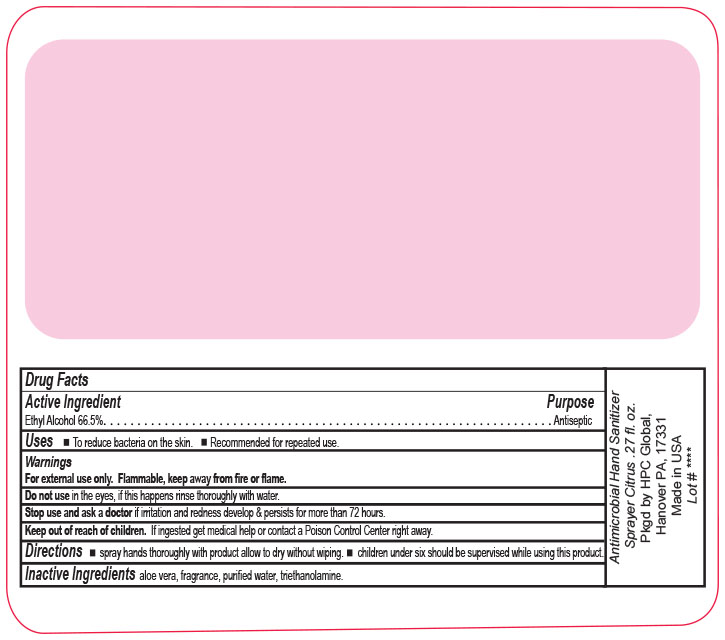 DRUG LABEL: Antimicrobial Hand Sanitizer
NDC: 51811-450 | Form: SPRAY
Manufacturer: Hanover Pen Corp dba HPC Global
Category: otc | Type: HUMAN OTC DRUG LABEL
Date: 20200630

ACTIVE INGREDIENTS: ALCOHOL 5.32 mL/8 mL
INACTIVE INGREDIENTS: TROLAMINE; ALOE VERA LEAF; WATER

Antimicrobial Hand Sanitizer 8ml Citrus Scent

Active Ingredient

Ethyl Alcohol 66.5 percent

Purpose

Anticeptic

Uses

- To decrease bacteria on the skin.
- Recommended for repeated use.

Warnings

For external use only. Flammable, keep away from fire or flame.

Do not use in the eyes, if this happens rinse thoroughly with water.

Stop use and ask a doctor if irritation or redness develops and persists for more thanb 72 hours.

Keep out of reach of children.

If ingested get medical help or contact a Poison Control Cener right away.

Directions

- spray hands throughly with product allow to dry without wiping.
- children under six should be supervised while using this product.

Inactive Indredients

aloe vera, fragrance, purified water, triethanolamine